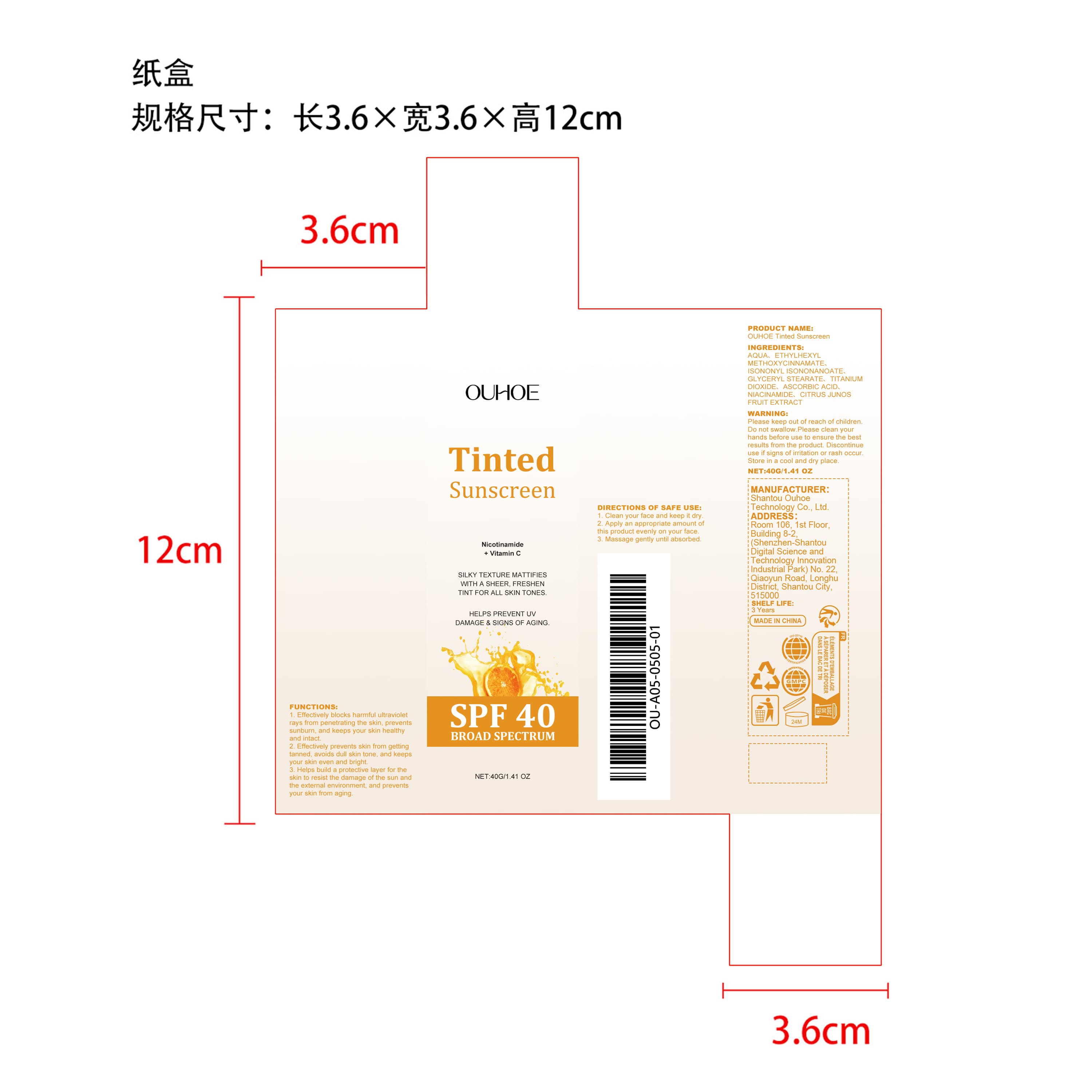 DRUG LABEL: OUHOE Tinted Sunscreen
NDC: 85163-012 | Form: CREAM
Manufacturer: Shantou Ouhoe Technology Co., Ltd.
Category: otc | Type: HUMAN OTC DRUG LABEL
Date: 20251205

ACTIVE INGREDIENTS: CITRUS JUNOS FRUIT 0.008 mg/40 mg
INACTIVE INGREDIENTS: ASCORBIC ACID 0.12 mg/40 mg; ISONONYL ISONONANOATE 1.6 mg/40 mg; ETHYLHEXYL METHOXYCINNAMATE 2 mg/40 mg; TITANIUM DIOXIDE 0.4 mg/40 mg; NIACINAMIDE 0.008 mg/40 mg; AQUA 35.264 mg/40 mg; GLYCERYL STEARATE 0.6 mg/40 mg

ACTIVE INGREDIENT

CITRUS JUNOS FRUIT EXTRACT

PURPOSE

1. Effectively blocks harmful ultraviolet rays from penetrating the skin, prevents sunburn, and keeps your skin healthy and intact.

2. Effectively prevents skin from getting tanned, avoids dull skin tone, and keeps your skin even and bright.

3. Helps build a protective layer for the skin to resist the damage of the sun and the external environment, and prevents your skin from aging.

WHEN USING

1. Clean your face and keep it dry.

2. Apply an appropriate amount of this product evenly on your face.

3. Massage gently until absorbed.

WARNINGS

Please keep out of reach of children. Do not swallow.Please clean your hands before use to ensure the best results from the product. Discontinue use if signs of irritation or rash occur. Store in a cool and dry place.

DO NOT USE

Discontinue use if signs of irritation or rash occur.

STOP USE

Discontinue use if signs of irritation or rash occur.

KEEP OUT OF REACH OF CHILDREN

Please keep out of reach of children. Do not swallow.

STORAGE AND HANDLING

Store in a cool and dry place.

INACTIVE INGREDIENT

AQUA、ETHYLHEXYL METHOXYCINNAMATE、ISONONYL ISONONANOATE、GLYCERYL STEARATE、TITANIUM DIOXIDE、ASCORBIC ACID、NIACINAMIDE

INDICATIONS AND USAGE

Discontinue use if signs of irritation or rash occur.

DOSAGE AND ADMINISTRATION

Discontinue use if signs of irritation or rash occur.